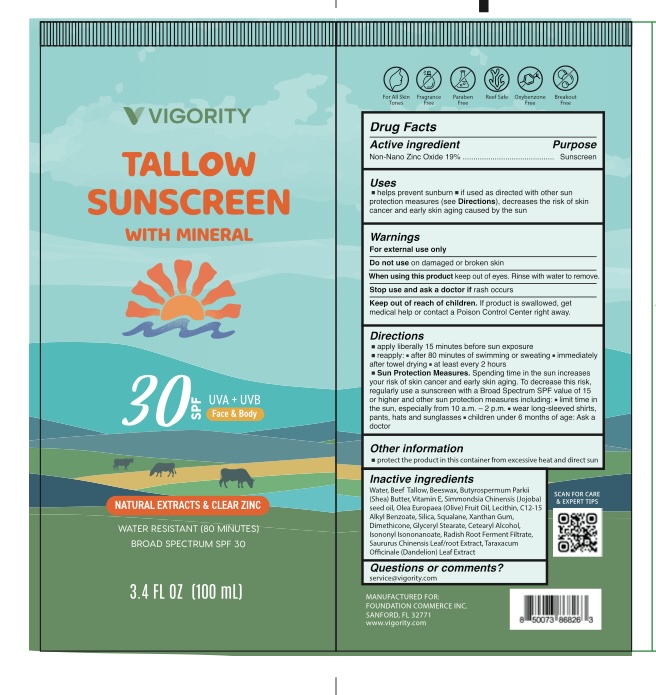 DRUG LABEL: Tallow Sunscreen SPF 30
NDC: 85739-004 | Form: CREAM
Manufacturer: FOUNDATION COMMERCE INC
Category: otc | Type: HUMAN OTC DRUG LABEL
Date: 20250731

ACTIVE INGREDIENTS: ZINC OXIDE 19 g/100 mL
INACTIVE INGREDIENTS: WATER; XANTHAN GUM; LECITHIN, SOYBEAN; ISONONYL ISONONANOATE; BEEF TALLOW; BUTYROSPERMUM PARKII (SHEA) BUTTER; SAURURUS CHINENSIS WHOLE; BEESWAX; LEUCONOSTOC/RADISH ROOT FERMENT FILTRATE; C12-15 ALKYL BENZOATE; SILICA; GLYCERYL STEARATE; CETEARYL ALCOHOL; TARAXACUM OFFICINALE LEAF; SQUALANE; DIMETHICONE; SIMMONDSIA CHINENSIS (JOJOBA) SEED OIL; TOCOPHEROL; OLEA EUROPAEA (OLIVE) FRUIT OIL

Initial Drug Listing - Vigority Tallow Sunscreen SPF30

ACTIVE INGREDIENT

Non-Nano Zinc Oxide 19%

PURPOSE

Sunscreen

INDICATIONS AND USAGE

- helps prevent sunburn
- if used as directed with other sun protection measures (see Directions), decreases the risk of skin cancer and early skin aging caused by the sun

WARNINGS

For external use only

Do not use on damaged or broken skin

When using this product keep out of eyes. Rinse with water to remove.

Stop use and ask a doctor if rash occurs

Keep out of reach of children. If product is swallowed, get medical help or contact a Poison Control Center right away.

DOSAGE AND ADMINISTRATION

- apply liberally 15 minutes before sun exposure
- reapply: - after 80 minutes of swimming or sweating - immediately after towel drying - at least every 2 hours
- Sun Protection Measures. Spending time in the sun increases your risk of skin cancer and early skin aging. To decrease this risk, regularly use a sunscreen with a Broad Spectrum SPF value of 15 or higher and other sun protection measures including: - limit time in the sun, especially from 10 a.m. - 2 p.m. - wear long-sleeved shirts, pants, hats and sunglasses - children under 6 months of age: Ask a doctor

OTHER SAFETY INFORMATION

protect the product in this container from excessive heat and direct sun

INACTIVE INGREDIENT

Water, Beef Tallow, Beeswax, Butyrospermum Parkii (Shea) Butter, Vitamin E, Simmondsia Chinensis (Jojoba) seed oil, Olea Europaea (Olive) Fruit Oil, Lecithin, C12-15 Alkyl Benzoate, Silica, Squalane, Xanthan Gum, Dimethicone, Glyceryl Stearate, Cetearyl Alcohol, Isononyl Isononanoate, Radish Root Ferment Filtrate, Saururus Chinensis Leaf/root Extract, Taraxacum Officinale (Dandelion) Leaf Extract

QUESTIONS

service@vigority.com